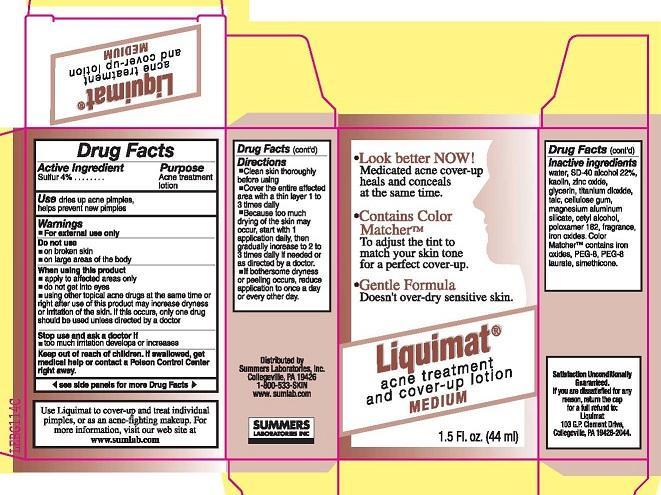 DRUG LABEL: LIQUIMAT
NDC: 11086-028 | Form: LIQUID
Manufacturer: Summers Laboratories Inc
Category: otc | Type: HUMAN OTC DRUG LABEL
Date: 20240327

ACTIVE INGREDIENTS: SULFUR 3 g/100 mL
INACTIVE INGREDIENTS: ALCOHOL 22 mL/100 mL; KAOLIN; ZINC OXIDE; GLYCERIN; TITANIUM DIOXIDE; WATER; TALC; CARBOXYMETHYLCELLULOSE SODIUM; MAGNESIUM ALUMINUM SILICATE; CETYL ALCOHOL; POLOXAMER 182; FERRIC OXIDE RED; FERRIC OXIDE YELLOW; POLYETHYLENE GLYCOL 400; PEG-8 LAURATE; DIMETHICONE

SUMMERS LABS (as PLD) - LIQUIMAT (11086-028)

ACTIVE INGREDIENT

SULFUR 4%

PURPOSE

ACNE TREATMENT LOTION

USE

DRIES UP ACNE PIMPLES, HELPS PREVENT NEW PIMPLES

WARNINGS

- FOR EXTERNAL USE ONLY

DO NOT USE

- ON BROKEN SKIN
- ON LARGE AREAS OF THE BODY

WHEN USING THIS PRODUCT

- APPLY TO AFFECTED AREAS ONLY
- DO NOT GET INTO EYES
- USING OTHER TOPICAL ACNE DRUGS AT THE SAME TIME OR RIGHT AFTER USE OF THIS PRODUCT MAY INCREASE DRYNESS OR IRRITATION OF THE SKIN. IF THIS OCCURS, ONLY ONE DRUG SHOULD BE USED UNLESS DIRECTED BY A DOCTOR

STOP USE AND ASK A DOCTOR IF

- TOO MUCH IRRITATION DEVELOPS OR INCREASES

KEEP OUT OF REACH OF CHILDREN. IF SWALLOWED, GET MEDICAL HELP OR CONTACT A POISON CONTROL CENTER RIGHT AWAY.

DIRECTIONS

- CLEAN SKIN THOROUGHLY BEFORE USING
- COVER THE ENTIRE AFFECTED AREA WITH A THIN LAYER 1 TO 3 TIMES DAILY
- BECAUSE TOO MUCH DRYING OF THE SKIN MAY OCCUR, START WITH 1 APPLICATION DAILY, THEN INCREASE TO 2 TO 3 TIMES DAILY IF NEEDED OR AS DIRECTED BY A DOCTOR.

INACTIVE INGREDIENTS

WATER, SD-40 ALCOHOL 22-PERCENT, KAOLIN, ZINC OXIDE, GLYCERIN, TITANIUM DIOXIDE, TALC, CELLULOSE GUM, MAGNESIUM ALUMINUM SILICATE, CETYL ALCOHOL, POLOXAMER 182, FRAGRANCE, IRON OXIDES. COLOR MATCHER CONTAINS IRON OXIDES, PEG-8, PEG-8 LAURATE, SIMETHICONE.